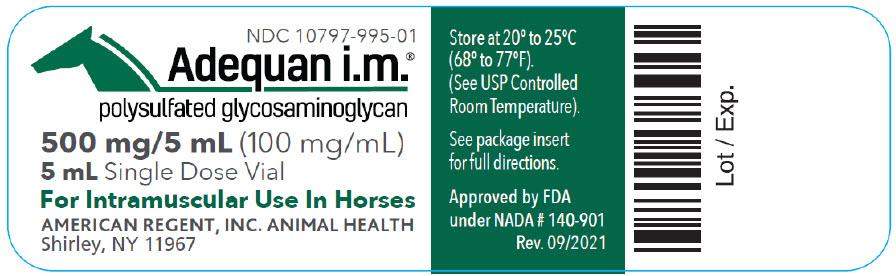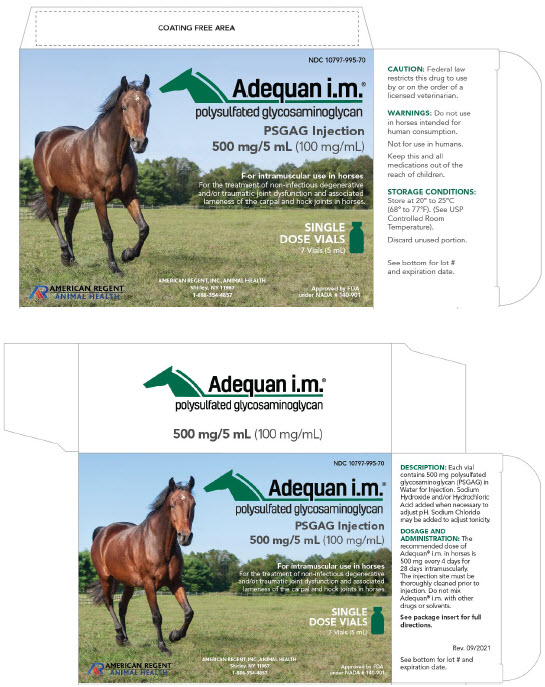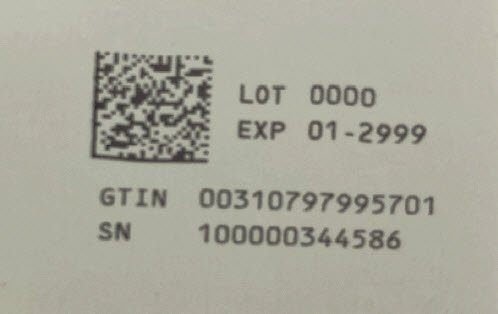 DRUG LABEL: Adequan i.m.
NDC: 10797-995 | Form: INJECTION, SOLUTION
Manufacturer: American Regent, Inc.
Category: animal | Type: PRESCRIPTION ANIMAL DRUG LABEL
Date: 20241007

ACTIVE INGREDIENTS: POLYSULFATED GLYCOSAMINOGLYCAN 100 mg/1 mL
INACTIVE INGREDIENTS: WATER

Adequan® i.m.

polysulfated glycosaminoglycan

SINGLE DOSE

Solution 500 mg/5 mL
For Intramuscular Use In Horses

CAUTION:

Federal law restricts this drug to use by or on the order of a licensed veterinarian.

DESCRIPTION:

Each 5 milliliters of Adequan® i.m. contains 500 mg of Polysulfated Glycosaminoglycan (PSGAG) and Water for Injection q.s. Sodium Hydroxide and/or Hydrochloric Acid added when necessary to adjust pH. Sodium Chloride may be added to adjust tonicity.

PHARMACOLOGY:

Polysulfated Glycosaminoglycan is chemically similar to the glycosaminoglycans in articular cartilage matrix. PSGAG is a potent proteolytic enzyme inhibitor and diminishes or reverses the pathologic processes of traumatic or degenerative joint disease which result in a net loss of cartilage matrix components. PSGAG improves joint function by reducing synovial fluid protein levels and increasing synovial fluid hyaluronic acid concentration in traumatized equine carpal and hock joints.

INDICATIONS:

Adequan® i.m. is recommended for the intramuscular treatment of non-infectious degenerative and/or traumatic joint dysfunction and associated lameness of the carpal and hock joints in horses.

DOSAGE AND ADMINISTRATION:

The recommended dose of Adequan® i.m. in horses is 500 mg every 4 days for 28 days intramuscularly. The injection site must be thoroughly cleansed prior to injection. Do not mix Adequan® i.m. with other drugs or solvents.

CONTRAINDICATIONS:

There are no known contraindications to the use of intramuscular Polysulfated Glycosaminoglycan.

WARNINGS:

Do not use in horses intended for human consumption. Not for use in humans. Keep this and all medications out of the reach of children.

PRECAUTIONS:

The safe use of Adequan® i.m. in horses used for breeding purposes, during pregnancy, or in lactating mares has not been evaluated.

ANIMAL SAFETY:

Toxicity studies were conducted in horses. Doses as high as 2,500 mg were administered intramuscularly to 6 horses twice a week for 12 weeks. This dosage is 5 times the recommended dosage and 3 times the recommended therapeutic regimen. Clinical observations revealed no soreness or swelling at the injection site or in the affected joint. No animal had any clinical or laboratory evidence of toxicity.

STORAGE CONDITIONS:

Store at 20°-25°C (68°-77°F); (See USP Controlled Room Temperature). Discard unused portion.

Dispose of spent needles in accordance with all federal, state and local environmental laws.

HOW SUPPLIED:

Adequan® i.m. solution, 500 mg/5 mL (100 mg/mL) in a 5 mL single dose glass vial.
NDC 10797-995-70 5 mL Single Dose Vials Packaged 7 vials per box

AMERICAN REGENT, INC.
ANIMAL HEALTH
Shirley, NY 11967
(1-888-354-4857)
Approved by FDA under NADA #140-901
Made in U.S.A.

IN 99501
Rev. 9/2021
MG # 44455

Container Label

NDC 10797-995-01
Adequan® i.m.
polysulfated glycosaminoglycan
500 mg/5 mL (100 mg/mL)
For Intramuscular Use In Horses
Store at 20°-25°C (68°-77°F) (See USP Controlled Room Temperature).
AMERICAN REGENT, INC. ANIMAL HEALTH
Shirley, NY 11967

Carton Labeling

NDC 10797-995-70

Adequani.m.®
polysulfated glycosaminoglycan
PSGAG Injection
500 mg/5 mL (100 mg/mL)

For the intramuscular use in horses.
For the treatment of non-infectious degenerative and/or traumatic joint dysfunction and associated lameness of the carpal and hock joint in horses.

SINGLE DOSE VIALS

7 Vials (5 mL each)

AMERICAN REGENT, INC., ANIMAL HEALTH
Shirley, NY 11967
(1-888-354-4857)
Approved by FDA under NADA # 140-901